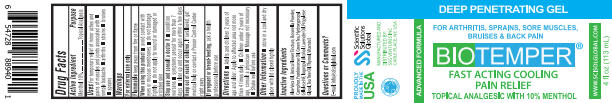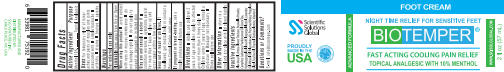 DRUG LABEL: Biotemper
NDC: 81376-001 | Form: GEL
Manufacturer: SSG Ventures Inc
Category: otc | Type: HUMAN OTC DRUG LABEL
Date: 20210421

ACTIVE INGREDIENTS: MENTHOL 1 g/10 mL
INACTIVE INGREDIENTS: PROPYLENE GLYCOL; ARNICA MONTANA; THYMOL; .ALPHA.-TOCOPHEROL ACETATE; ALOE VERA LEAF; CAMPHOR (NATURAL); HYDROXYPROPYL CELLULOSE, UNSPECIFIED; ISOPROPYL ALCOHOL; TEA TREE OIL; BOSWELLIA SACRA BARK; FRANKINCENSE OIL; GREEN TEA LEAF; LAVENDER OIL

Biotemper

PACKAGE LABEL

ACTIVE INGREDIENT

Menthol 10%.......................Topical Analgesic

PURPOSE

TOPICAL ANALGESIC WITH 10% MENTHOL

INDICATIONS AND USAGE

FOR ARTHRITIS, SPRAINS, SORE MUSCLES, BRUISES, & BACK PAIN

FAST ACTING COOLING PAIN RELIEF

WARNINGS

FOR EXTERNAL USE ONLY

KEEP OUT OF REACH OF CHILDREN.

IF SWALLOWED, GET MEDICAL HELP OR CONTACT A POISON CONTROL CENTER RIGHT AWAY

DOSAGE AND ADMINISTRATION

Adults & children 2 yrs of age and older: Apply to affected area not more than 4 times daily. Children under 2 years of age, consult a physician. Massage not necessary. Shake well before use.

INACTIVE INGREDIENT

Aloe Vera Oil, Arnica Flower Tincture, Boswellia Powder, Camphor, Frankincense Oil, Green Tea, Hydroxypropyl Cellulose NF, Isopropyl Alcohol, Lavender Oil, Propylene Glycol, Tea Tree Oil, Thymol, Vitamin E.

OTHER SAFETY INFORMATION

Store in a cool and dry place with lid closed